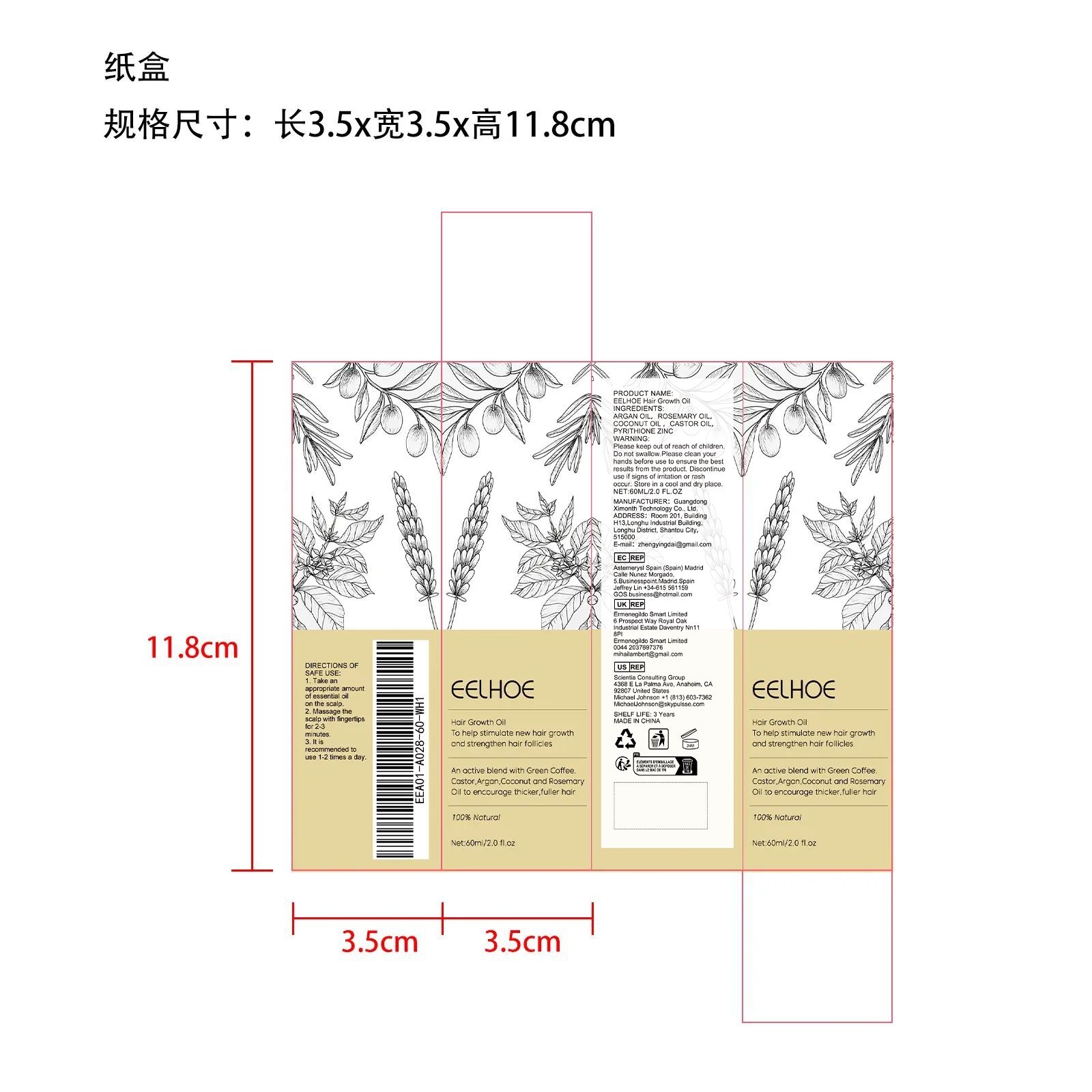 DRUG LABEL: EELHOE Hair Growth Oil
NDC: 84660-039 | Form: OIL
Manufacturer: Guangdong Ximonth Technology Co., Ltd.
Category: otc | Type: HUMAN OTC DRUG LABEL
Date: 20241006

ACTIVE INGREDIENTS: ARGAN OIL 12 mg/60 mg; CASTOR OIL 15 mg/60 mg; ROSEMARY OIL 6 mg/60 mg; COCONUT OIL 9 mg/60 mg
INACTIVE INGREDIENTS: PYRITHIONE ZINC 18 mg/60 mg

Active Ingredient(s)

ARGAN OIL，ROSEMARY OIL，COCONUT OIL ，CASTOR OIL

Purpose

To help stimulate new hair growthand strengthen hair follicles

Use

1. Take an appropriate amount of essential oil on the scalp.
2. Massage the scalp with fingertips for 2-3 minutes.
3. It is recommended to use 1-2 times a day.

Do not use

Discontinue use if signs of irritation or rash occur.

STOP USE

Discontinue use if signs of irritation or rash occur.

KEEP OUT OF REACH OF CHILDREN

Please keep out of reach of children. Do not swallow.

Warnings

Please keep out of reach of children.Do not swallow.Please clean your hands before use to ensure the best results from the product.Discontinue use if signs of irritation or rash occur.Store in a cool and dry place.

STORAGE AND HANDLING

Avoid freezing and excessive heat above 40C (104F) ）
Store in a cool and dry place.

INACTIVE INGREDIENT

PYRITHIONE ZINC